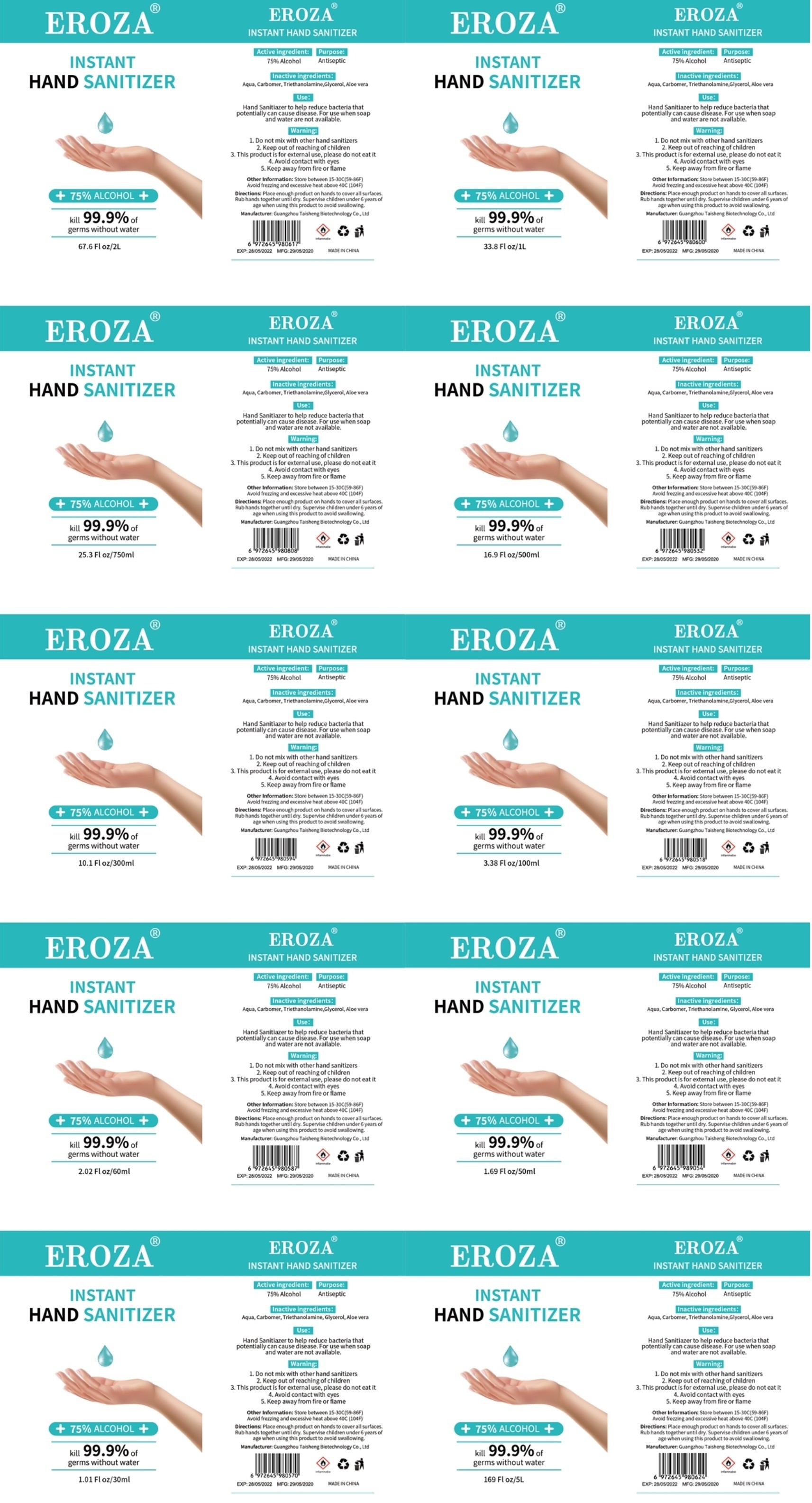 DRUG LABEL: HAND SANITIZER
NDC: 79603-001 | Form: GEL
Manufacturer: Guangzhou Taisheng Biotechnology Co., Ltd.
Category: otc | Type: HUMAN OTC DRUG LABEL
Date: 20200713

ACTIVE INGREDIENTS: ALCOHOL 75 mL/100 mL
INACTIVE INGREDIENTS: ALOE VERA LEAF; TROLAMINE; GLYCERIN; CARBOMER HOMOPOLYMER, UNSPECIFIED TYPE; WATER

HAND SANITIZER

Active Ingredient(s)

75%Alcohol

Purpose

Antiseptic

Use

Hand Sa nitiazer to help reduce bacteria that potentially can cause d isease. For use when soap and water are not available.

Warnings

l.Do not mix with other hand sanitizers
2.Keep out of reaching of children
3.This product is for externa I use, please do not eat it
4.Avoid contact with eyes
5.Keep away from fire or flame

Do not use

/

WHEN USING

/

STOP USE

/

Keep out of reach of children.

Directions

Place enough product on hands to cover all .surfaces. Rub hands together until dry. Supervise children under6 years of age when using this product to avoid swallowing.

Other information

Store between 15-30C(59-86F)
Avoid frezzing and excessive heat above 40C (104F)

Inactive ingredients

Aqua, Carbomer, Triethanolamine, Glycerol, Aloe vera